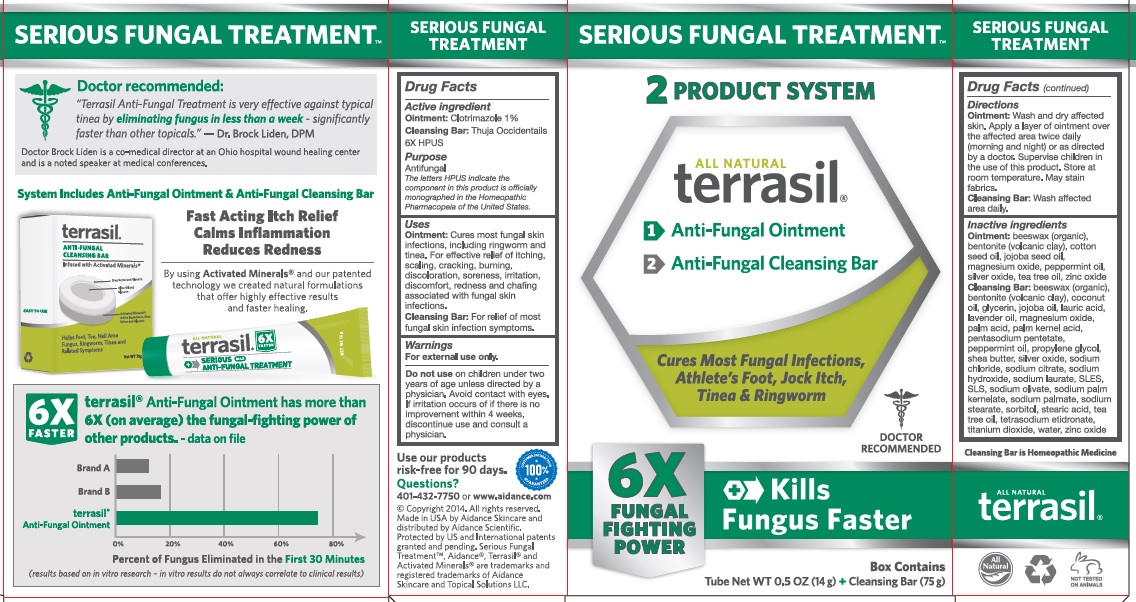 DRUG LABEL: Terrasil SERIOUS FUNGAL TREATMENT
NDC: 24909-155 | Form: KIT | Route: TOPICAL
Manufacturer: Aidance Skincare & Topical Solutions, LLC
Category: otc | Type: HUMAN OTC DRUG LABEL
Date: 20241125

ACTIVE INGREDIENTS: CLOTRIMAZOLE 1 g/100 g; THUJA OCCIDENTALIS WHOLE 6 [hp_X]/1 g
INACTIVE INGREDIENTS: BENTONITE; COTTONSEED OIL; JOJOBA OIL; MAGNESIUM OXIDE; PEPPERMINT OIL; SILVER OXIDE; TEA TREE OIL; WHITE WAX; ZINC OXIDE; BENTONITE; COCONUT OIL; GLYCERIN; JOJOBA OIL; LAURIC ACID; LAVENDER OIL; MAGNESIUM OXIDE; PALM ACID; PALM KERNEL ACID; PENTASODIUM PENTETATE; PEPPERMINT OIL; PROPYLENE GLYCOL; SHEA BUTTER; SILVER OXIDE; SODIUM CHLORIDE; SODIUM CITRATE; SODIUM HYDROXIDE; SODIUM LAURATE; SODIUM LAURETH SULFATE; SODIUM PALM KERNELATE; SODIUM PALMATE; SODIUM STEARATE; SORBITOL; STEARIC ACID; TEA TREE OIL; TITANIUM DIOXIDE; ETIDRONATE TETRASODIUM; WATER; WHITE WAX; ZINC OXIDE

24909-155 terrasil Serious Fungal Treatment

Active Ingredient

Ointment: Clotrimazole 1%

Cleansing Bar: Thuja Occidentalis 6X HPUS

The letters HPUS indicate the component(s) in this product is (are) officially monographed in the Homeopathic Pharmacopeia of the United States.

Purpose

Antifungal

Uses

Ointment: Cures most fungal skin infections, including ringworm and tinea. For effective relief of itching, scaling, cracking, burning, discoloration, soreness, irritation, discomfort, redness and chafing associated with fungal skin infections.

Cleansing Bar: For relief of most fungal skin infection symptoms.

Warnings

For external use only.
Do not useon children under two years of age unless directed by a physician. Avoid contact with the eyes. If irritation occurs or if there is no improvement within 4 weeks, discontinue use and consult a physician.

Directions

Ointment:Wash and dry affected skin. Apply a layer of oinment over the affected area twice daily (morning and night) or as directed by a doctor. Supervise children in the use of this product. Store at room temperature. May stain fabrics.

Cleansing Bar:Wash affected area daily.

Inactive Ingredients

Ointment:beeswax (organic), bentonite (volcanic clay), cotton seed oil, jojoba seed oil, magnesium oxide, peppermint oil, silver oxide, tea tree oil, zinc oxide.

Cleansing Bar: beeswax (organic), bentonite (volcanic clay), coconut oil, glycerin, jojoba seed oil, lauric acid, lavender oil, magnesium oxide, palm acid, palm kernel acid, pentasodium pentetate, peppermint oil, propylene glycol, shea butter, silver oxide, sodium chloride, sodium citrate, sodium hydroxide, sodium laurate, SLES, SLS, sodium olvate, sodium palm kernelate, sodium palmate, sodium stearate, sorbitol, stearic acid, tea tree oil, tetrasodium etidronate, titanium dioxide, water, zinc oxide.

PRINCIPAL DISPLAY PANEL

SERIOUS FUNGAL TREATMENT
2 PRODUCT SYSTEM

All Natural
terrasil®
1> Anti-Fungal Ointment
2> Anti-Fungal Cleansing Bar

Cures most Fungal Infections, Athlete’s Foot, Jock Itch, Tinea & Ringworm